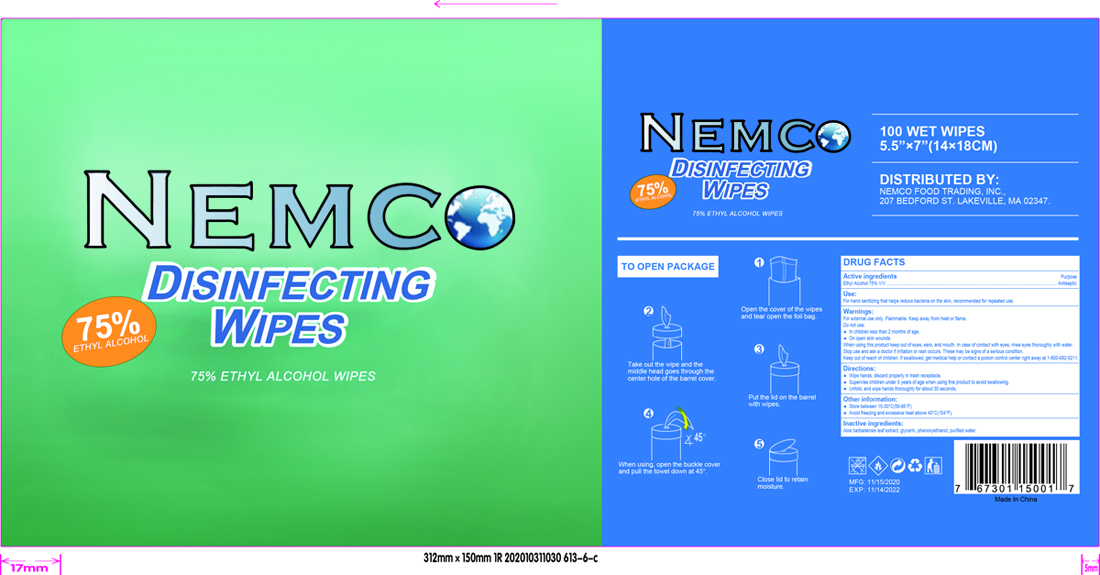 DRUG LABEL: sanitizing wipes
NDC: 80172-001 | Form: CLOTH
Manufacturer: Nemco Food Trading, Inc.
Category: otc | Type: HUMAN OTC DRUG LABEL
Date: 20201102

ACTIVE INGREDIENTS: ALCOHOL 0.75 mL/1 g
INACTIVE INGREDIENTS: ALOE VERA LEAF; WATER; GLYCERIN; PHENOXYETHANOL

sanitizing wipes

Active Ingredients

Ethyl Alcohol 75% Purpose: Antiseptic

Use

For hand sanitizing that helps reduce bacteria on the skin, recommended for repearted use.

Warnings

For external use only-highly flammable. Keep away from fire or flame.

Do not use

- In children less than 2 months of age.
- On open skin wounds

When using this product keep out of eyes, ears, and mouth. In case of contact with eyes, rinse eyes thoroughly with water.

Stop use and ask a doctor if irritation or rash occurs. These may be signs of a serious condition.

Keep out of reach of children. If swallowed, contact a poison control center right away at 1-800-682-9211

Do not use

- In children less than 2 months of age.
- On open skin wounds

WHEN USING THIS PRODUCT

keep out of eyes, ears, and mouth. In case of contact with eyes, rinse eyes thoroughly with water.

Stop use and ask a doctor if irritation or rash occurs. These may be signs of a serious condition.

Keep out of reach of children.

If swallowed, contact a poison control center right away at 1-800-682-9211

Directions

-Wipe hands, discard properly in trash receptacle.

-Supervise children under 6 years of age when using this product to avoid swallowing

-Unfold, and wipe hands thoroughly for about 30 seconds

Other information

Store between 15-30C (59-86F)

Avoid freezing and excesssive heat above 40C (104F)

Inactive ingredients

Aloe barbadensis leaf extract, glycerin, phenoxyethanol, purified water

Package Label - Principal Display Panel

100 PCS NDC: 80172-001-01

NEMCO

DISINFECTING

WIPES

75% ETHYL ALCOHOL WIPES

100 WET WIPES

5.5'' * 7' (14 * 18CM)